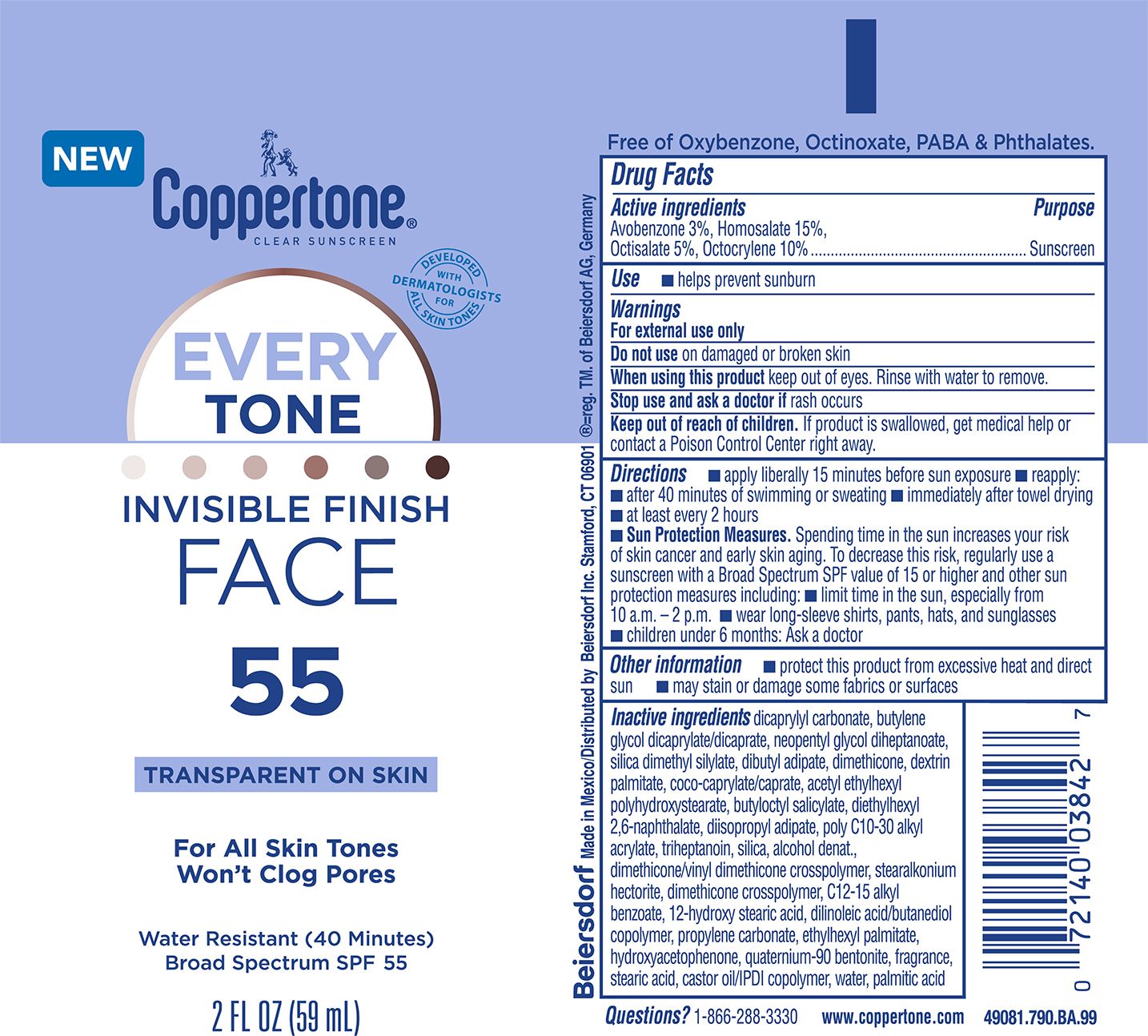 DRUG LABEL: Coppertone EveryTone Face Sunscreen SPF 55
NDC: 66800-1094 | Form: LOTION
Manufacturer: Beiersdorf Inc
Category: otc | Type: HUMAN OTC DRUG LABEL
Date: 20251217

ACTIVE INGREDIENTS: HOMOSALATE 15 g/100 g; OCTOCRYLENE 10 g/100 g; OCTISALATE 5 g/100 g; AVOBENZONE 3 g/100 g
INACTIVE INGREDIENTS: ACRYLATES/C10-30 ALKYL ACRYLATE CROSSPOLYMER (60000 MPA.S); TRIHEPTANOIN; COCO-CAPRYLATE/CAPRATE; HYDROGENATED CASTOR OIL; ALKYL (C12-15) BENZOATE; 12-HYDROXYSTEARIC ACID; ETHYLHEXYL PALMITATE; DIMETHICONE/VINYL DIMETHICONE CROSSPOLYMER (SOFT PARTICLE); PROPYLENE CARBONATE; PALMITIC ACID; DIETHYLHEXYL 2,6-NAPHTHALATE; DIISOPROPYL ADIPATE; ISOPHORONE DIISOCYANATE; STEARIC ACID; DILINOLEIC ACID/BUTANEDIOL COPOLYMER; WATER; NEOPENTYL GLYCOL DIHEPTANOATE; DEXTRIN PALMITATE (CORN; 20000 MW); HYDROXYACETOPHENONE; FRAGRANCE CLEAN ORC0600327; ALCOHOL; BUTYLENE GLYCOL DICAPRYLATE/DICAPRATE; DICAPRYLYL CARBONATE; DIMETHICONE; QUATERNIUM-90 BENTONITE; BUTYLOCTYL SALICYLATE; SILICA DIMETHYL SILYLATE; DIBUTYL ADIPATE; SILICON DIOXIDE

EveryTone SPF 55 Lotion

Active ingredients

Avobenzone 3%, Homosalate 15%, Octisalate 5%, Octocrylene 10%

Purpose

Sunscreen

Use

■ helps prevent sunburn

Warnings

For external use only

Do not useon damaged or broken skin

WHEN USING

When using this productkeep out of eyes. Rinse with water to remove.

Stop use and ask a doctor ifrash occurs

Keep out of reach of children.If product is swallowed, get medical help or contact a Poison Control Center right away.

Directions

■ apply liberally 15 minutes before sun exposure

■ reapply:

■ after 40 minutes of swimming or sweating

■ immediately after towel drying

■ at least every 2 hours

■ Sun Protection Measures.Spending time in the sun increases your risk of skin cancer and early skin aging. To decrease this risk, regularly use a sunscreen with a Broad Spectrum SPF value of 15 or higher and other sun protection measures including:

■ limit time in the sun, especially from 10 a.m. – 2 p.m.

■ wear long-sleeve shirts, pants, hats, and sunglasses

■ children under 6 months: Ask a doctor

Other information

■ protect this product from excessive heat and direct sun

■ may stain or damage some fabrics or surfaces

Inactive ingredients

dicaprylyl carbonate, butylene glycol dicaprylate/dicaprate, neopentyl glycol diheptanoate, silica dimethyl silylate, dibutyl adipate, dimethicone, dextrin palmitate, coco-caprylate/caprate, acetyl ethylhexyl polyhydroxystearate, butyloctyl salicylate, diethylhexyl 2,6-naphthalate, diisopropyl adipate, poly C10-30 alkyl acrylate, triheptanoin, silica, alcohol denat., dimethicone/vinyl dimethicone crosspolymer, stearalkonium hectorite, dimethicone crosspolymer, C12-15 alkyl benzoate, 12-hydroxy stearic acid, dilinoleic acid/butanediol copolymer, propylene carbonate, ethylhexyl palmitate, hydroxyacetophenone, quaternium-90 bentonite, fragrance, stearic acid, castor oil/IPDI copolymer, water, palmitic acid

Questions?

1-866-288-3330

PACKAGE LABEL

Coppertone®Clear Sunscreen

EveryTone

Invisible Finish Face

55

Transparent on Skin

For All Skin Tones

Won't Clog Pores

Water Resistant (40 Minutes)

Broad Spectrum SPF 55